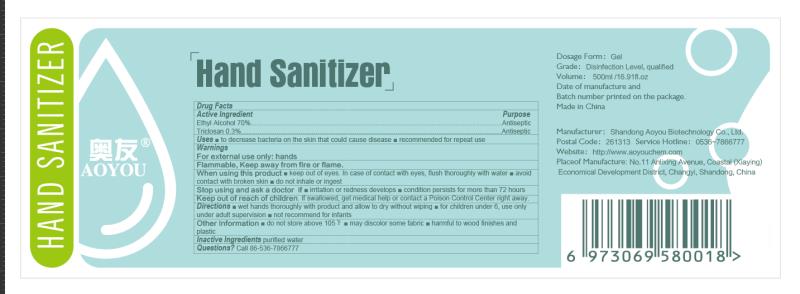 DRUG LABEL: Hand Sanitizer
NDC: 75118-002 | Form: GEL
Manufacturer: Shandong Aoyou Biotechnology Co.,Ltd
Category: otc | Type: HUMAN OTC DRUG LABEL
Date: 20200510

ACTIVE INGREDIENTS: ALCOHOL 70 mL/100 mL
INACTIVE INGREDIENTS: TRICLOSAN; WATER

Hand Sanitizer

Active Ingredient

Ethyl Alcohol 70%

Purpose

Antiseptic

Uses

to decrease bacteria on the skin that could cause disease . recommended for repeat use

Warnings

For external use only:hands

Flammable, Keep away from fire or flame.

When using this product

keep out of eyes.In case of contact with eyes, flush thoroughly with water.avoid

contact with broken skin.do not inhale or ingest

STOP USE

Stop using and ask a doctor if irritation or redness develops.condition persists for more than 72 hours.

Keep out of reach of children.lf swallowed,get medical help or contact a Poison Control Center right away.

Directions

wet hands thoroughly with product and allow to dry without wiping.for children under 6,use only

under adult supervision. not recommend for infants.

Other Information

do not store above 105°F

may discolor some fabric

harmful to wood finishes and plastic.

Inactive Ingredients

purified water